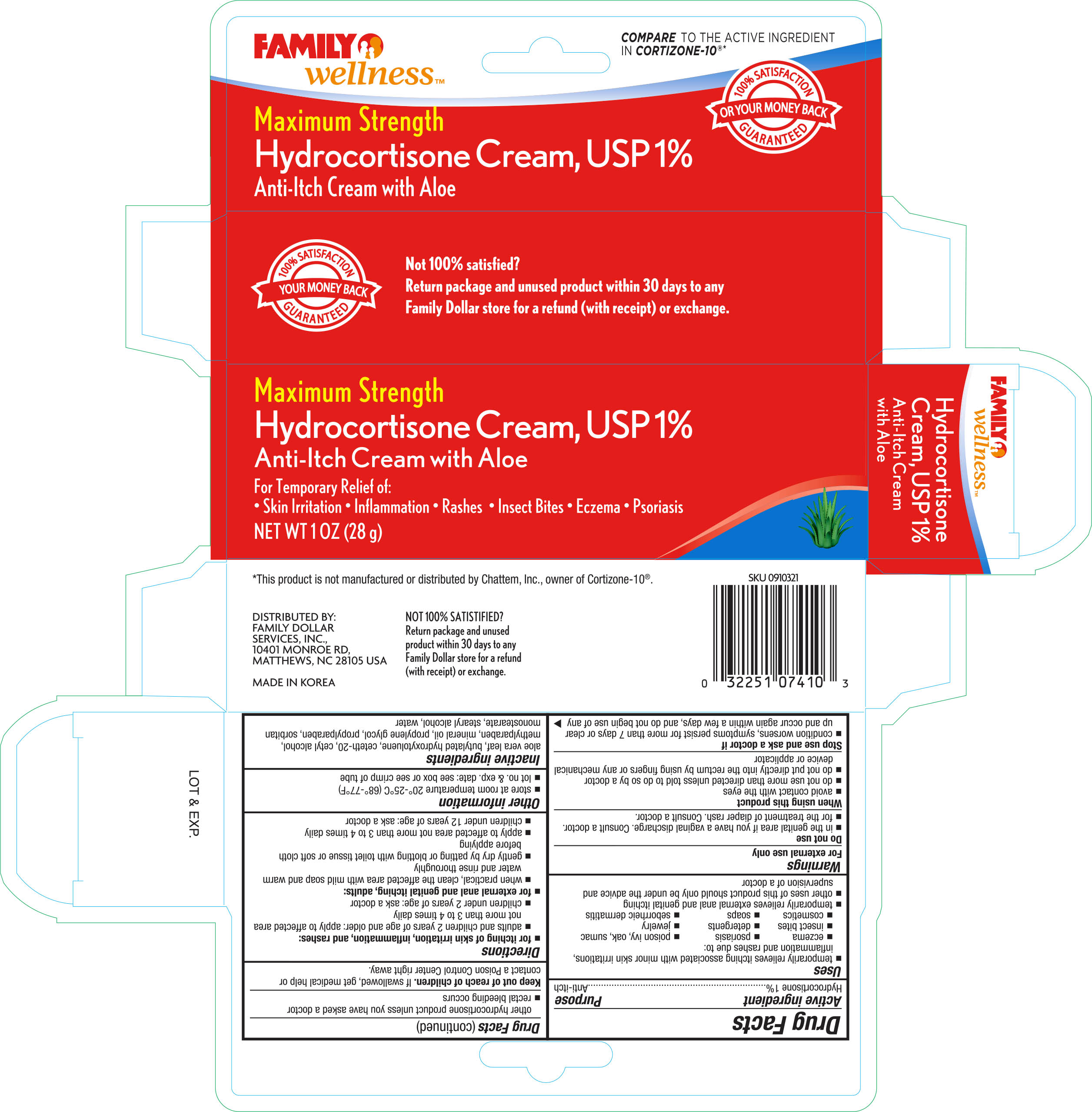 DRUG LABEL: Family Wellness Maximum Strength Hydrocortisone
NDC: 55319-074 | Form: CREAM
Manufacturer: Family Dollar
Category: otc | Type: HUMAN OTC DRUG LABEL
Date: 20160919

ACTIVE INGREDIENTS: HYDROCORTISONE 1 g/100 g
INACTIVE INGREDIENTS: ALOE VERA LEAF; BUTYLATED HYDROXYTOLUENE; CETETH-20; CETYL ALCOHOL; METHYLPARABEN; MINERAL OIL; PROPYLENE GLYCOL; PROPYLPARABEN; SORBITAN MONOSTEARATE; STEARYL ALCOHOL; WATER

Active ingredient Purpose

Hydrocortisone, USP 1%.......................................Anti-Itch

Uses

for the temporary relief of itching associated with minor skin irritations, inflammation, and rashes due to:

- eczema
- insect bites
- poison ivy
- poison oak
- poison sumac
- soaps
- jewelry
- detergents
- cosmetics
- psoriasis
- seborrhea dermatitis
- temporarily relieves external anal and genital itching
- other uses for this product should be only under the advice and supervision of a doctor

Warnings

For external use only

Do not use

- in the genital area if you have a vaginal discharge. Consult a doctor.
- for the treatment of diaper rash. Consult a doctor.

When using this product

- avoid contact with the eyes
- do not use more than directed unless told to do so by a doctor
- do not put this product into the rectum by using finger or any mechanical device or applicator

Stop use and ask a doctor if

- condition worsens, symptoms persist for more than 7 days or clear up and occur again within a few days, and do not begin use of any other hydrocortisone product unless you have asked a doctor
- rectal bleeding occurs

Keep out of reach of children

If swallowed, get medical help or contact a Poison Control Center right away.

Directions

- for itching of skin irritation, inflammation, and rashes:
- adults and children 2 years of age and older: apply to affected area not more than 3 to 4 times daily
- children under 2 years of age: ask a doctor

Other information

- Store at room temperature 20°-25°C (68°-77°F)
- lot no. & exp. date: see box or see crimp of tube

Inactive ingredients

aloe vera leaf, butylated hydroxytoluene, ceteth-20, cetyl alcohol, methylparaben, mineral oil, propylene glycol, propylparaben, sorbitan monostearate, stearyl alcohol, water

DOSAGE AND ADMINISTRATION

Distributed By:

Family Dollar Services, Inc.

10401 Monroe Rd.

Matthews, NC 28105 USA

Made in Korea